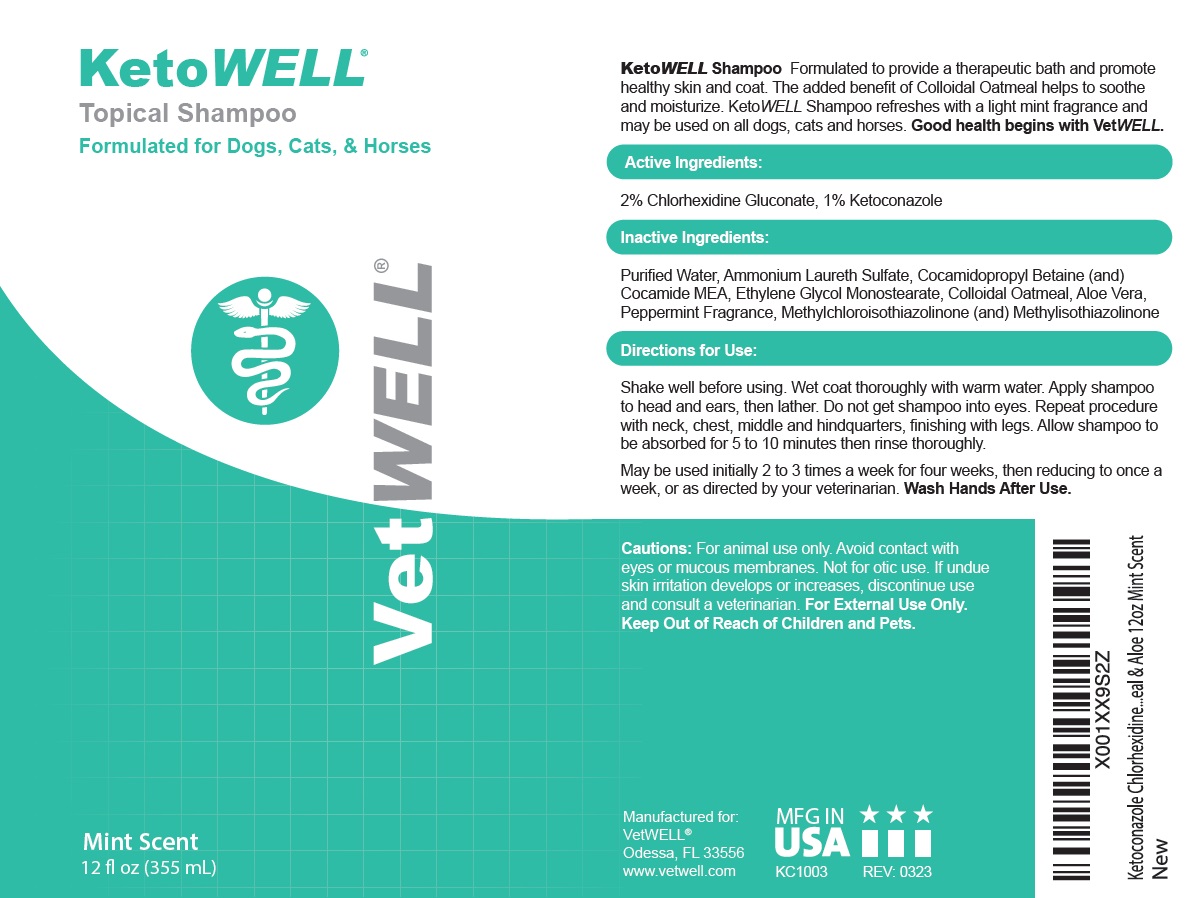 DRUG LABEL: VetWELL KetoWELL
NDC: 86090-012 | Form: SHAMPOO
Manufacturer: Pet MD Brands, LLC
Category: animal | Type: OTC ANIMAL DRUG LABEL
Date: 20230908

ACTIVE INGREDIENTS: CHLORHEXIDINE GLUCONATE 2 g/100 mL; KETOCONAZOLE 1 g/100 mL
INACTIVE INGREDIENTS: WATER; AMMONIUM LAURETH-3 SULFATE; COCAMIDOPROPYL BETAINE; COCO MONOETHANOLAMIDE; GLYCOL STEARATE; OATMEAL; ALOE VERA LEAF; PEPPERMINT; METHYLCHLOROISOTHIAZOLINONE; METHYLISOTHIAZOLINONE

VetWELL® KetoWELL® Topical Shampoo

Active Ingredients:

2% Chlorhexidine Gluconate, 1% Ketoconazole

INDICATIONS AND USAGE

KetoWELL Shampoo Formulated to provide a therapeutic bath and promote healthy skin and coat. The added benefit of Colloidal Oatmeal helps to soothe and moisturize. KetoWELL Shampoo refreshes with a light mint fragrance and may be used on all dogs, cats and horses. Good health begins with VetWELL.

Inactive Ingredients:

Purified Water, Ammonium Laureth Sulfate, Cocamidopropyl Betaine (and) Cocamide MEA, Ethylene Glycol Monostearate, Colloidal Oatmeal, Aloe Vera, Peppermint Fragrance, Methylchloroisothiazolinone (and) Methylisothiazolinone

Directions for Use:

Shake well before using. Wet coat thoroughly with warm water. Apply shampoo to head and ears, then lather. Do not get shampoo into eyes. Repeat procedure with neck, chest, middle and hindquarters, finishing with legs. Allow shampoo to be absorbed for 5 to 10 minutes then rinse thoroughly.

May be used initially 2 to 3 times a week for four weeks, then reducing to once a week, or as directed by your veterinarian. Wash Hands After Use.

Cautions:

For animal use only. Avoid contact with eyes or mucous membranes. Not for otic use. If undue skin irritation develops or increases, discontinue use and consult a veterinarian. For External Use Only. Keep Out of Reach of Children and Pets.

Formulated for Dogs, Cats, & Horses

Mint Scent

Manufactured for:
VetWELL®
Odessa, FL 33556
www.vetwell.com

MFG IN USA